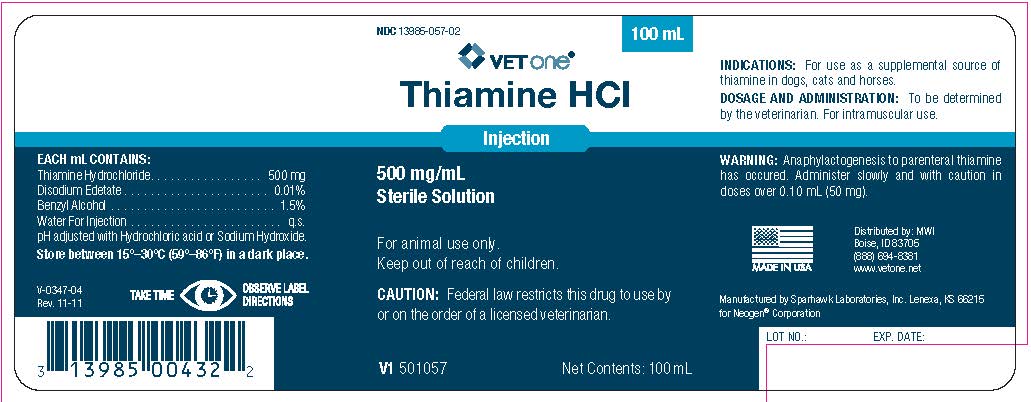 DRUG LABEL: Thiamina HCI
NDC: 13985-057 | Form: INJECTION
Manufacturer: MWI/VetOne
Category: animal | Type: PRESCRIPTION ANIMAL DRUG LABEL
Date: 20231213

ACTIVE INGREDIENTS: THIAMINE HYDROCHLORIDE 500 mg/1 mL
INACTIVE INGREDIENTS: EDETATE DISODIUM .1 mg/1 mL; BENZYL ALCOHOL .015 mL/1 mL; WATER

Thiamine HCI
Injection
500mg/mL
Sterile Solution

Indications:

For use as a supplemental source of thiamine in dogs, cats and horses.

Each mL Contains:

Thiamine Hydrochloride..........................500 mg

Disodium Edetate..............................0.01% w/v

Benzyle Alcohol (as preservative)..........1.5% v/v

Water for Injection......................................q.s.

pH adjusted with Hydrochloric acid or Sodium Hydroxide.

Dosage and Administration:

To be determined by the veterinarian. For intramuscular use.

Warning:

Anaphylactogenesis to parental thiamine has occurred. Administer slowly and with caution in doses over 0.10 mL (50mg)

STORAGE AND HANDLING

Store between 15º–30ºC (59º–86ºF) in a dark place.

Manufactured by Sparhawk Laboratories, Lenexa, KS 66215

for Neogen® Corporation

Principal Display Panel

THIAMINE HCI

Injection

500 mg/mL

Sterile Solution

For animal use only.

Keep out of reach of children.

Caution: Federal law restricts this drug to use by or on the order of a licensed veterinarian